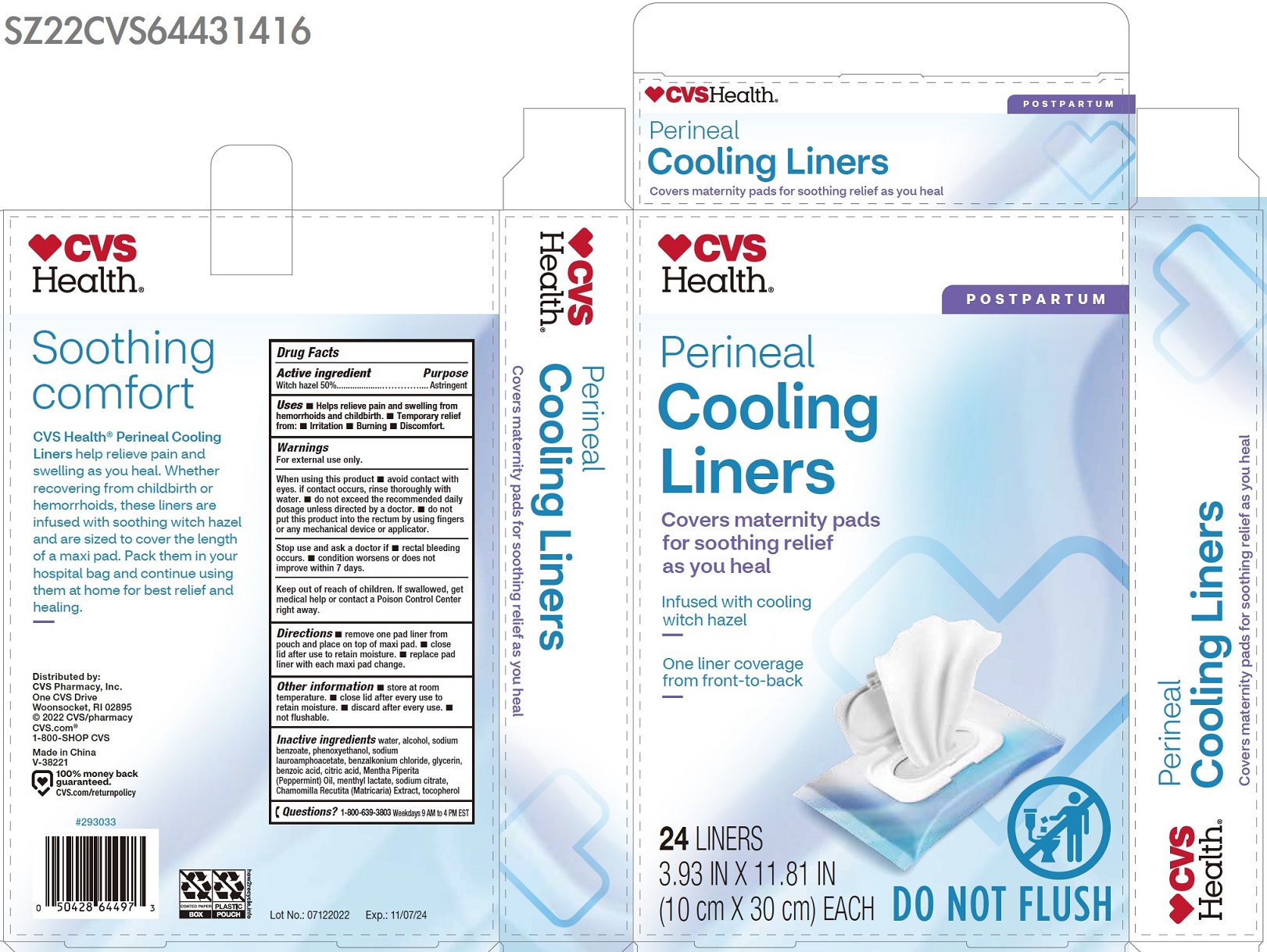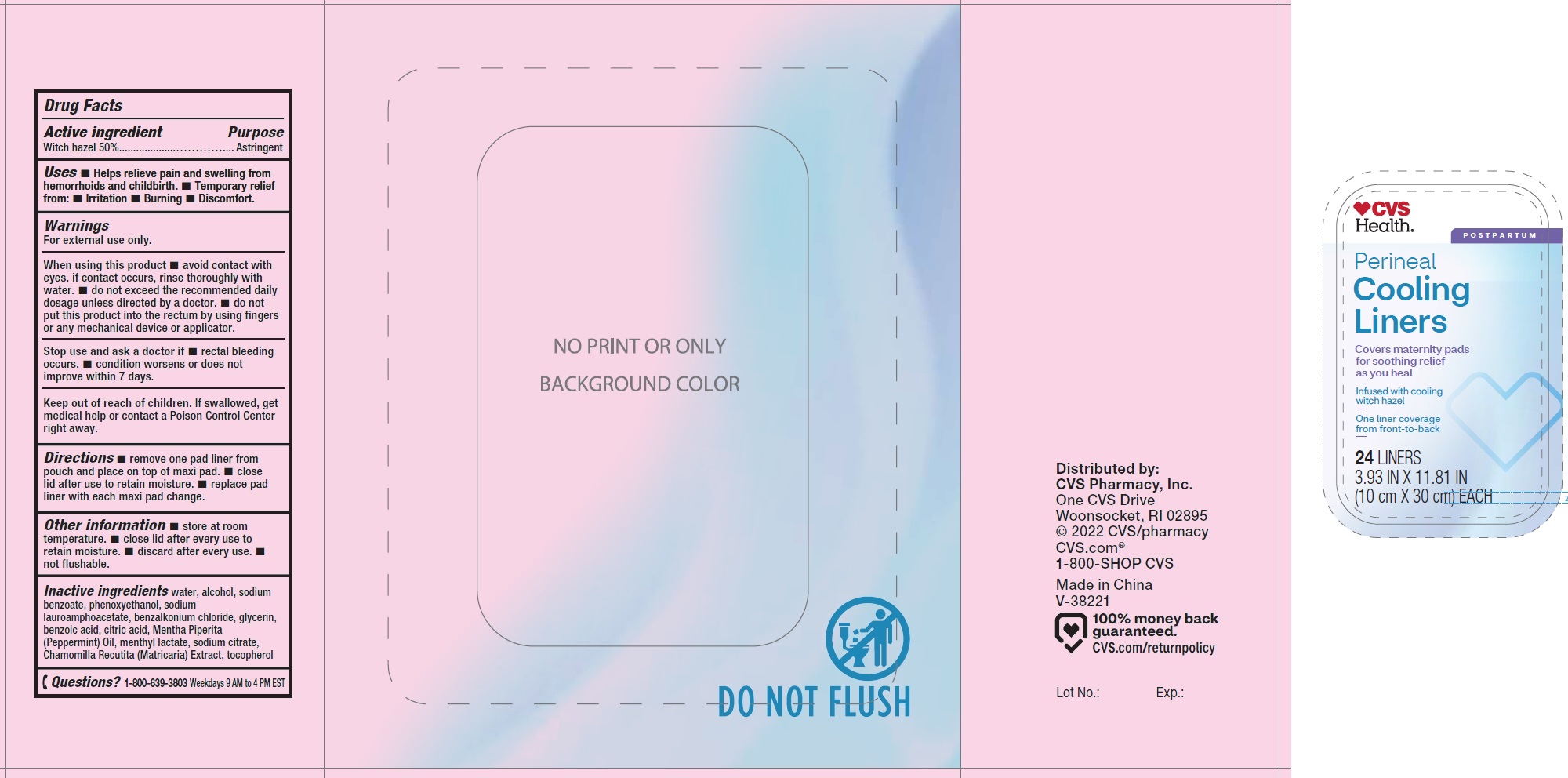 DRUG LABEL: Perineal Cooling Liners
NDC: 51316-716 | Form: SWAB
Manufacturer: CVS Pharmacy
Category: otc | Type: HUMAN OTC DRUG LABEL
Date: 20250225

ACTIVE INGREDIENTS: WITCH HAZEL 500 mg/1 g
INACTIVE INGREDIENTS: WATER; ALCOHOL; SODIUM BENZOATE; PHENOXYETHANOL; SODIUM LAUROAMPHOACETATE; BENZALKONIUM CHLORIDE; GLYCERIN; BENZOIC ACID; CITRIC ACID MONOHYDRATE; PEPPERMINT OIL; MENTHYL LACTATE, (-)-; SODIUM CITRATE; MATRICARIA CHAMOMILLA WHOLE; TOCOPHEROL

Perineal Cooling Liners

Active ingredient

Witch hazel 50%

Purpose

Astringent

Uses

- Helps relieve pain and swelling from hemorrhoids and childbirth.
- Temporary relief from:
- Irritation
- Burning
- Discomfort.

Warnings

For external use only.

When using this product

- avoid contact with eyes. if contact occurs, rinse thoroughly with water.
- do not exceed the recommended daily dosage unless directed by a doctor.
- do not put this product into the rectum by using fingers or any mechanical device or applicator.

Stop use and ask a doctor if

- rectal bleeding occurs.
- condition worsens or does not improve within 7 days.

Keep out of reach of children.

If swallowed, get medical help or contact a Poison Control Center right away.

Directions

- remove one pad liner from pouch and place on top of maxi pad.
- close lid after use to retain moisture.
- replace pad liner with each maxi pad change.

Other information

- store at room temperature.
- close lid after every use to retain moisture.
- discard after every use.
- not flushable.

Inactive ingredients

water, alcohol, sodium benzoate, phenoxyethanol, sodium lauroamphoacetate, benzalkonium chloride, glycerin, benzoic acid, citric acid, Mentha Piperita (Peppermint) Oil, menthyl lactate, sodium citrate, Chamomilla Recutita (Matricaria) Extract, tocopherol

Questions?

1-800-639-3803 Weekdays 9 AM to 4 PM EST